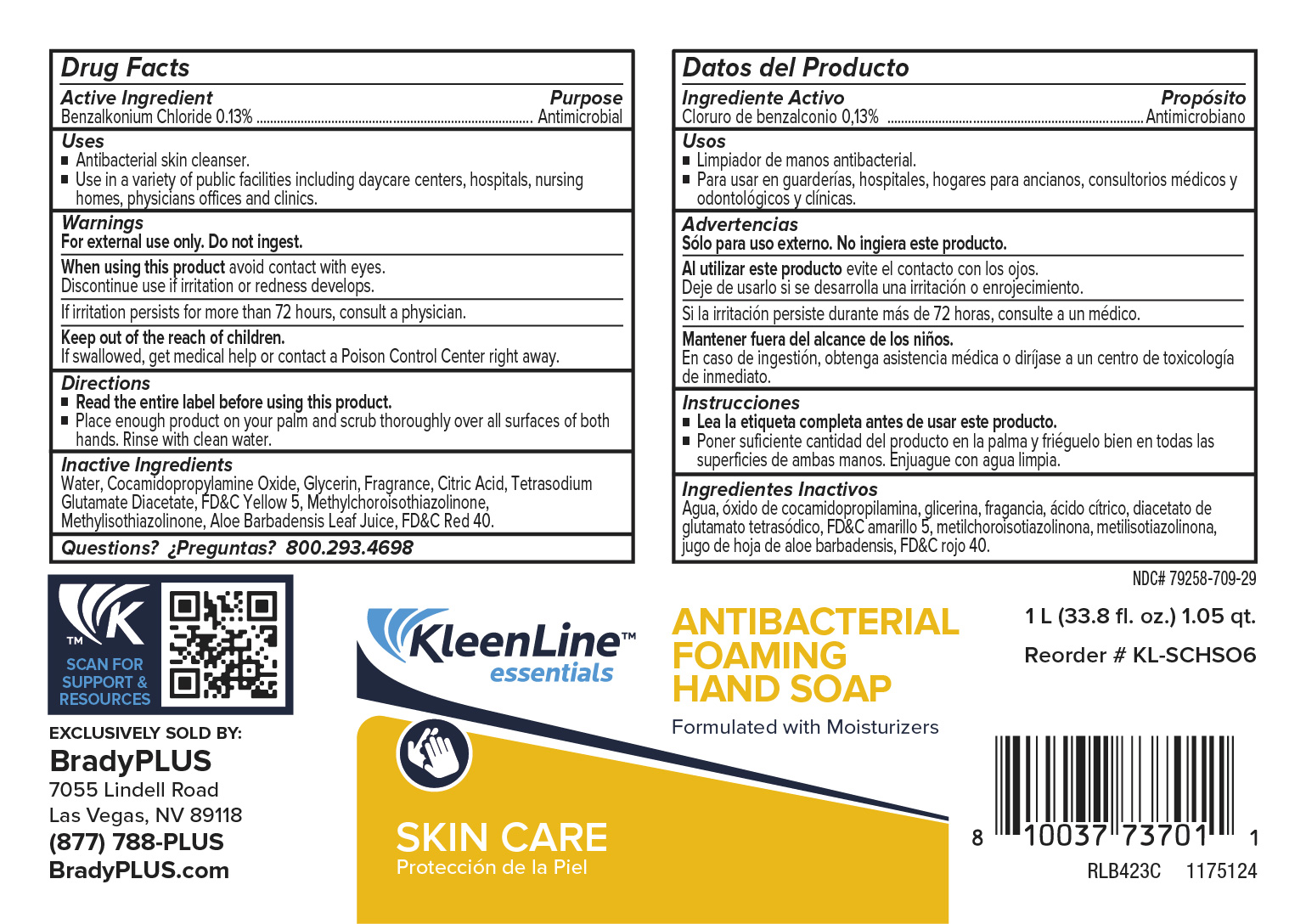 DRUG LABEL: KleenLine Essentials Antibacterial Foaming HandSoap
NDC: 79258-709 | Form: LIQUID
Manufacturer: Brady Industries
Category: otc | Type: HUMAN OTC DRUG LABEL
Date: 20241216

ACTIVE INGREDIENTS: BENZALKONIUM CHLORIDE 0.13 mg/1 mL
INACTIVE INGREDIENTS: WATER; FD&C YELLOW NO. 5; ANHYDROUS CITRIC ACID; GERANIOL; ALLYL HEPTANOATE; CAPRYLYL/CAPRYL GLUCOSIDE; GLYCERIN; TETRASODIUM EDTA; HYDROGEN PEROXIDE; MAGNESIUM NITRATE; 2-TERT-BUTYLCYCLOHEXYL ACETATE; 2,6-DIMETHYLOCTAN-2-OL; FD&C RED NO. 40; ALCOHOL; 4-CYCLOHEXYL-2-METHYL-2-BUTANOL; LIMONENE, (+)-; LINALOOL, (+/-)-; ALOE BARBADENSIS LEAF; SODIUM BENZOATE; CITRAL

KleenLine Essentials Antibacterial Foaming Hand Soap

directions

Read entire label before using this product

Place enough product on your palms and rub thoroughly over all surfaces of both hands Rinse with clean water.

ingredients

water, Caprylyl/Capryl Glucoside, Tetrasodium EDTA, Glycerin, Sodium Benzoate, Fragrance, Citric Acid, FD&C Yellow 5, Aloe Barbadensis Leaf Juice, FD&C REd 40

INSTRUCTIONS FOR USE

Read teh entire label before using this product

Palce enough product on your palm and scrub thoroughly over all surfaces of both hands. Rinse with clean water

ACTIVE INGREDIENT

Benzalkonium Chloride 0.13%

Keep out of reach of children

If swallowed, get medical help or Poison Control Center rgiht away.

PURPOSE

Antimicrobial

WARNINGS

For external use only, Do not ingest

When using this product avoid contact wiht eyes

Discontinue use if irritation or redness developes

If irritation pesists longer than 72 hours, consult a physician

DOSAGE AND ADMINISTRATION

Place enough product on your palm and scrub thoroughlyover all surfaces of both hands. Rinse with clean water

INDICATIONS AND USAGE

Antibacterial skin cleanser

use in a variety of publicfacilites including daycare centers, hospitals, nursing homes, phyicians offices and clinics